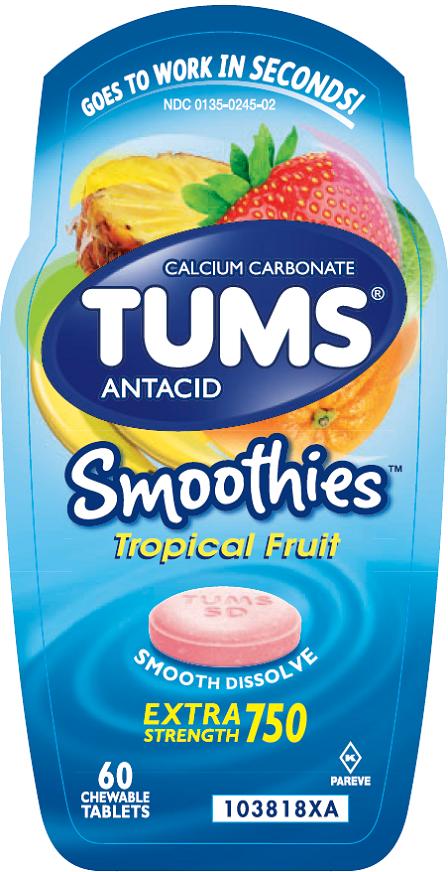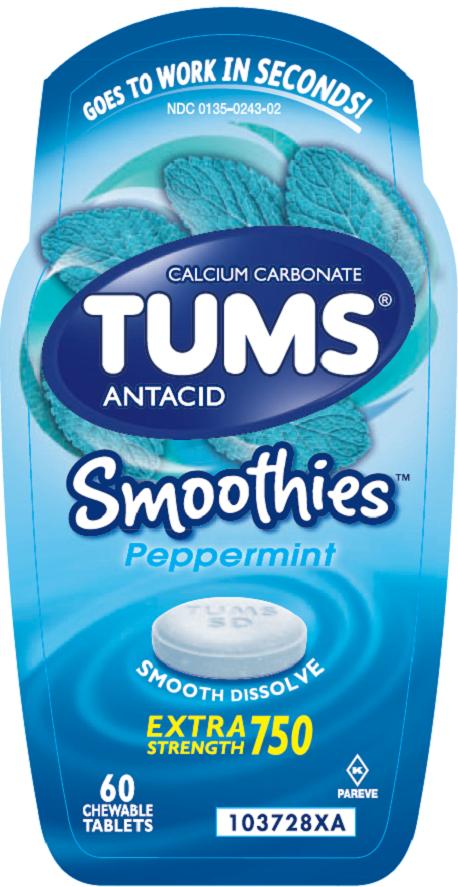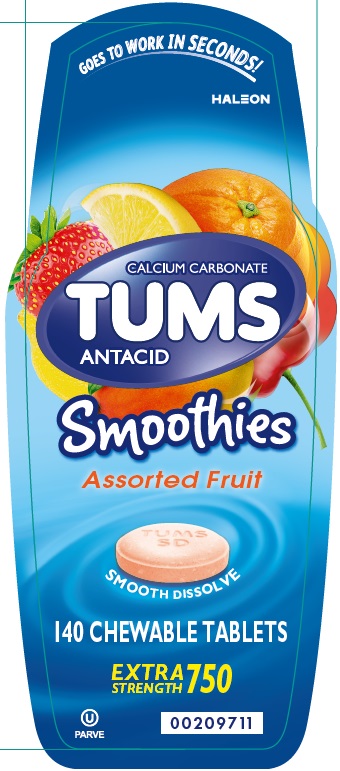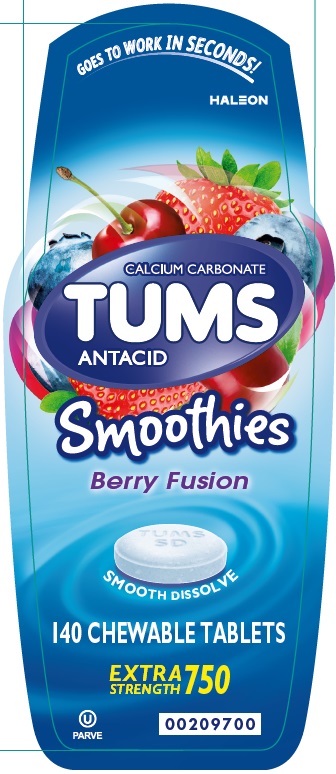 DRUG LABEL: TUMS
NDC: 0135-0246 | Form: TABLET, CHEWABLE
Manufacturer: Haleon US Holdings LLC
Category: otc | Type: HUMAN OTC DRUG LABEL
Date: 20250226

ACTIVE INGREDIENTS: CALCIUM CARBONATE 750 mg/1 1
INACTIVE INGREDIENTS: ACACIA; ADIPIC ACID; CALCIUM STEARATE; DEXTROSE, UNSPECIFIED FORM; FD&C BLUE NO. 1 ALUMINUM LAKE; FD&C RED NO. 40 ALUMINUM LAKE; FD&C YELLOW NO. 5 ALUMINUM LAKE; FD&C YELLOW NO. 6 ALUMINUM LAKE; GUAR GUM; MICROCRYSTALLINE CELLULOSE; SORBITOL; SOYBEAN

Drug Facts

Active ingredient (per tablet)

Calcium Carbonate 750 mg

Purpose

Antacid

Uses

relieves

- heartburn
- acid indigestion
- sour stomach
- upset stomach associated with these symptoms

Warnings

Ask a doctor or pharmacist before use if you are

presently taking a prescription drug. Antacids may interact with certain prescription drugs.

When using this product

- do not take more than 10 tablets in 24 hours
- if pregnant do not take more than 6 tablets in 24 hours
- do not use the maximum dosage for more than 2 weeks, except under the advice and supervision of a doctor

Directions

- adults and children 12 years of age and over: chew 2 – 4 tablets as symptoms occur, or as directed by a doctor. Chew or crush tablets completely before swallowing.
- do not take for symptoms that persist for more than 2 weeks unless advised by a doctor

Other information

- each tablet contains: elemental calcium 300 mg
- store below 25oC (77oF). Keep the container tightly closed.

Other information (Assorted Fruit)

- each tablet contains: elemental calcium 300 mg
- store below 25oC (77oF). Keep the container tightly closed.
- contains FD&C Yellow No. 5 (tartrazine) as a color additive

Inactive ingredients (Assorted Fruit)

acacia, adipic acid, calcium stearate, dextrose, FD&C blue no. 1 aluminum lake, FD&C red no. 40 aluminum lake, FD&C yellow no. 5 aluminum lake (tartrazine), FD&C yellow no. 6 aluminum lake, flavors, guar gum, microcrystalline cellulose, sorbitol

Contains: soy

Inactive ingredients (Berry Fusion)

acacia, adipic acid, calcium stearate, dextrose, FD&C blue no. 1 aluminum lake, FD&C red no. 40 aluminum lake, flavors, guar gum, microcrystalline cellulose, sorbitol

Contains: soy

Inactive ingredient (Assorted Tropical Fruit)

adipic acid, corn starch, dextrose, FD&C blue #1 lake, FD&C red #40 lake, FD&C yellow #6 lake, flavors, guar gum, magnesium stearate, maltodextrin, microcrystalline cellulose, sorbitol, sucrose

Contains: soy

Inactive ingredients (Peppermint)

corn starch, dextrose, flavors, guar gum, magnesium stearate, maltodextrin, microcrystalline cellulose, sorbitol, sucrose

Questions?

1-800-897-7535

Generic Section (Assorted Fruit and Berry Fusion)

Do not use if printed inner safety seal under cap is broken or missing.

Gluten-Free

Principal Display Panel (Assorted Fruit)

GOES TO WORK IN SECONDS!

CALCIUM CARBONATE

TUMS

ANTACID

Smoothies

Assorted Fruit

SMOOTH DISSOLVE

140 CHEWABLE TABLETS

EXTRA STRENGTH 750

PARVE

Principal Display Panel (Berry Fusion)

GOES TO WORK IN SECONDS!

CALCIUM CARBONATE

TUMS

ANTACID

Smoothies

Berry Fusion

SMOOTH DISSOLVE

140 CHEWABLE TABLETS

EXTRA STRENGTH 750

PARVE

Principal Display Panel (Tropical Fruit)

NDC 0135-0245-02

TUMS®

CALCIUM CARBONATE

ANTACID

SmoothiesTM

Tropical Fruit

SMOOTH DISSOLVE

EXTRA STRENGTH 750

GOES TO WORK IN SECONDS!

60 CHEWABLE TABLETS

PAREVE

Safety sealed – Do not use if printed inner seal beneath cap is missing or broken.

Principal Display Panel (Peppermint)

NDC 0135-0243-02

TUMS®

CALCIUM CARBONATE

ANTACID

SmoothiesTM

Peppermint

SMOOTH DISSOLVE

EXTRA STRENGTH 750

GOES TO WORK IN SECONDS!

60 CHEWABLE TABLETS

PAREVE

Safety sealed – Do not use if printed inner seal beneath cap is missing or broken.